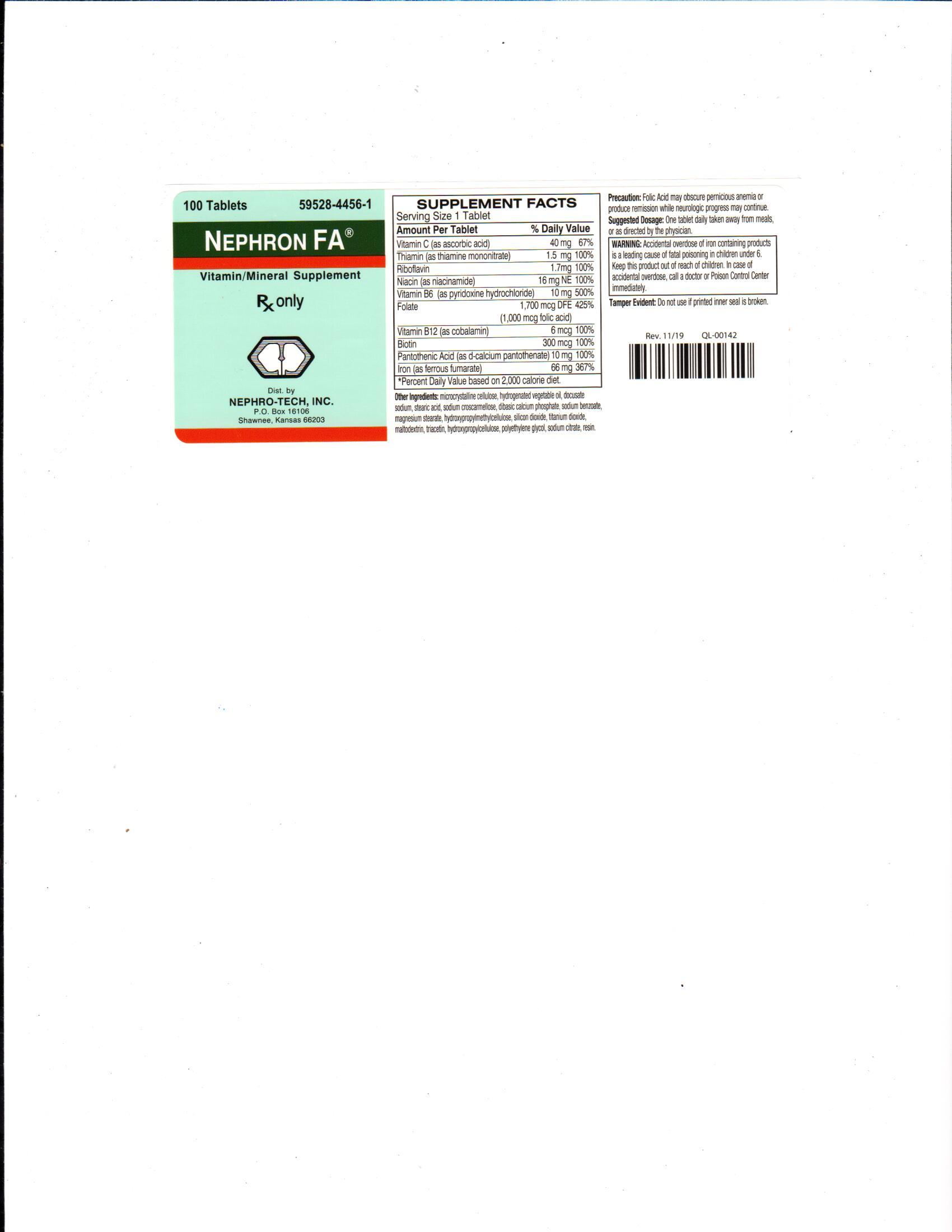 DRUG LABEL: Nephron FA
NDC: 59528-4456 | Form: TABLET, COATED
Manufacturer: Nephro-Tech, Inc.
Category: prescription | Type: HUMAN PRESCRIPTION DRUG LABEL
Date: 20210708

ACTIVE INGREDIENTS: IRON 66 mg/1 1; ASCORBIC ACID 40 mg/1 1; NIACINAMIDE 20 mg/1 1; PYRIDOXINE HYDROCHLORIDE 10 mg/1 1; PANTOTHENIC ACID 10 mg/1 1; RIBOFLAVIN 1.7 mg/1 1; THIAMINE 1.5 mg/1 1; FOLIC ACID 1 mg/1 1; Biotin .3 mg/1 1; COBALAMIN .006 mg/1 1

Nephron FA
multi-vitamin/mineral supplement with ascorbic acid, thiamine mononitrate, riboflavin, niacinamide, pyridoxine hydrochloride, folic acid, cyanocabalimin, biotin, pantothenic acid and ferrous fumarate, film-coated

Description

Nephron FA is a prescription folic acid supplement with additional nutrients for kidney dialysis patients. Nephron FA is an elongated, white, film coated tablet imprinted with NT and scored on one side, plain on the other.

Precaution

Folic Acid may obscure pernicious anemia or produce remission while neurologic progress may continue.

Suggested Dosage

One tablet daily taken away from meals, or as directed by the physician.

Package Label/Principal Display Panel

Nephron FA label

59528-4456-1

Rx Only

Nephron FA

Vitamin/Mineral Supplement

100 tablets